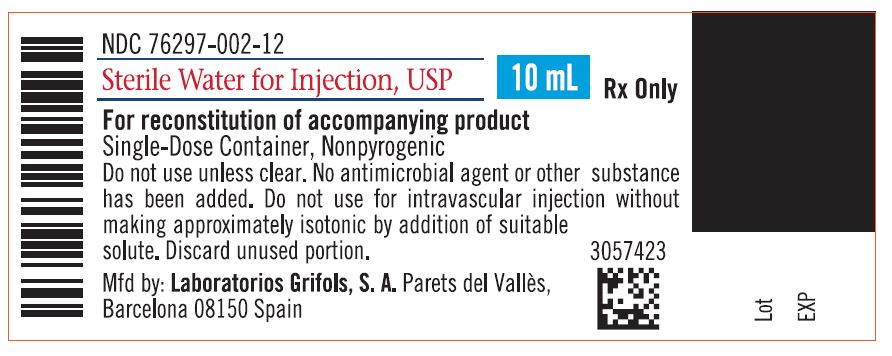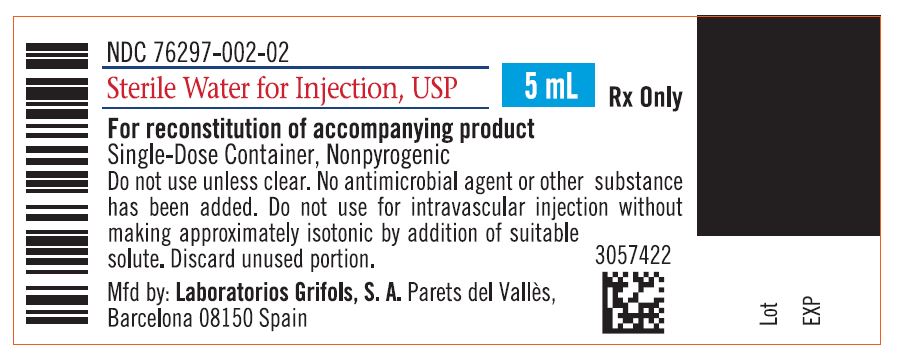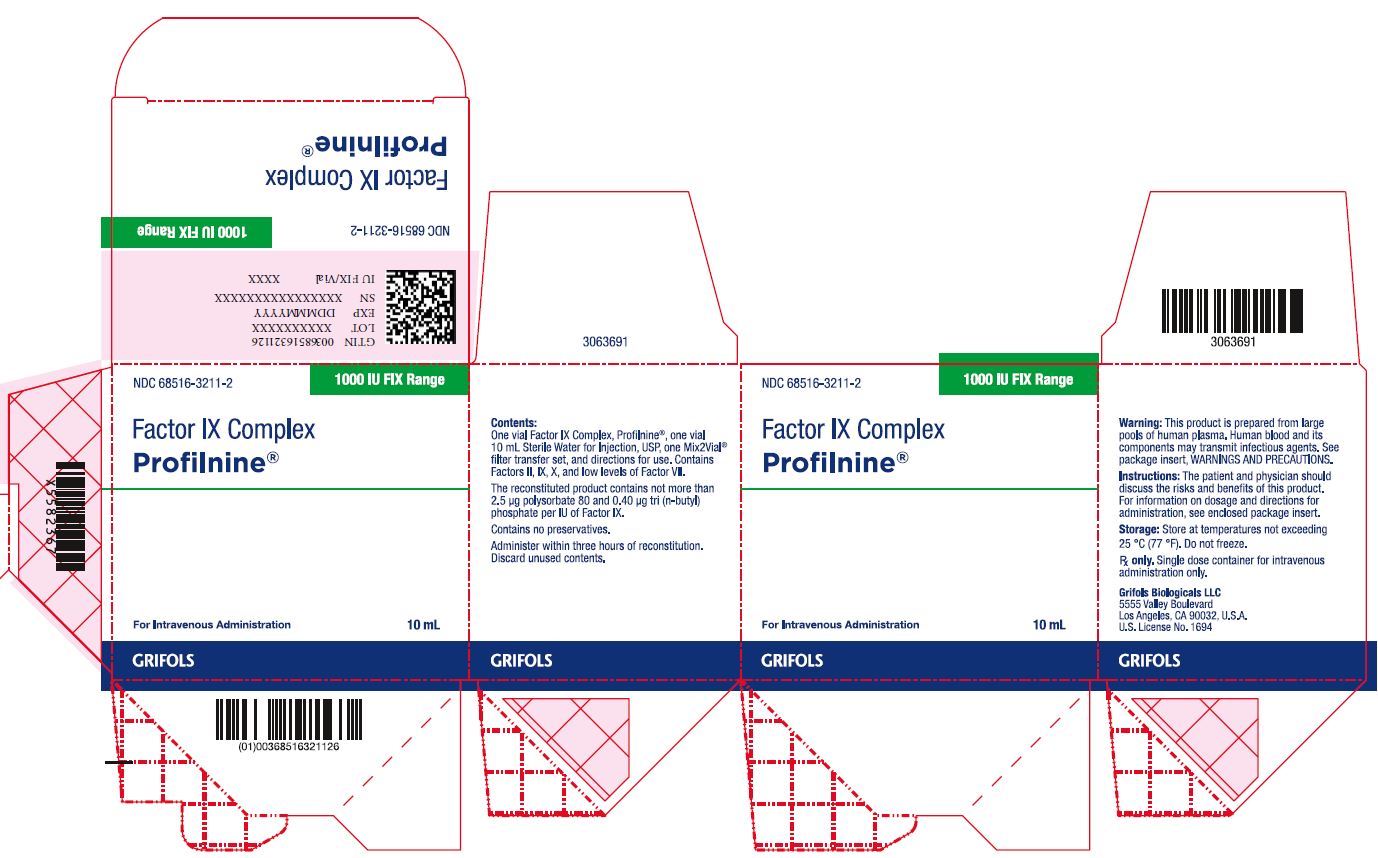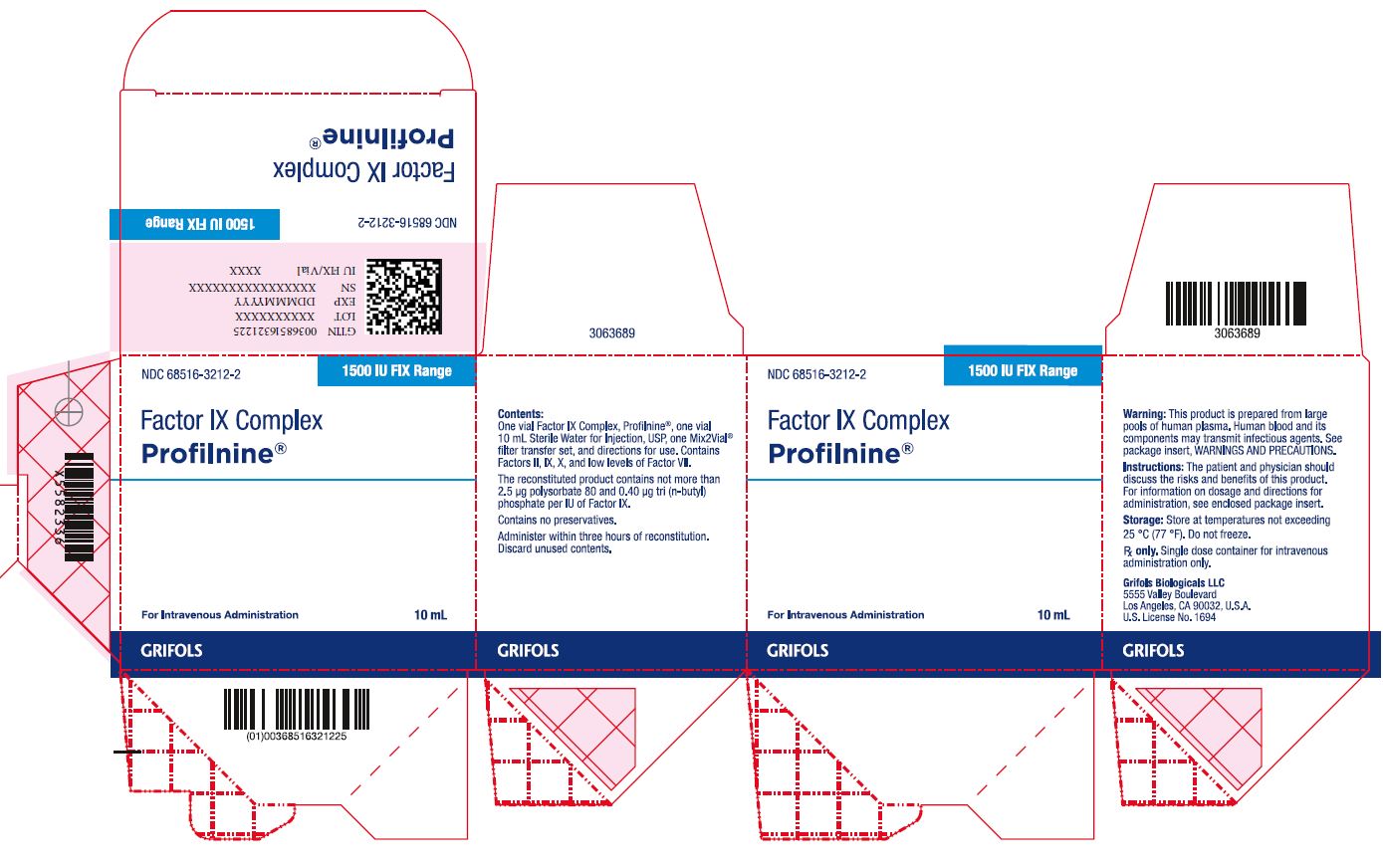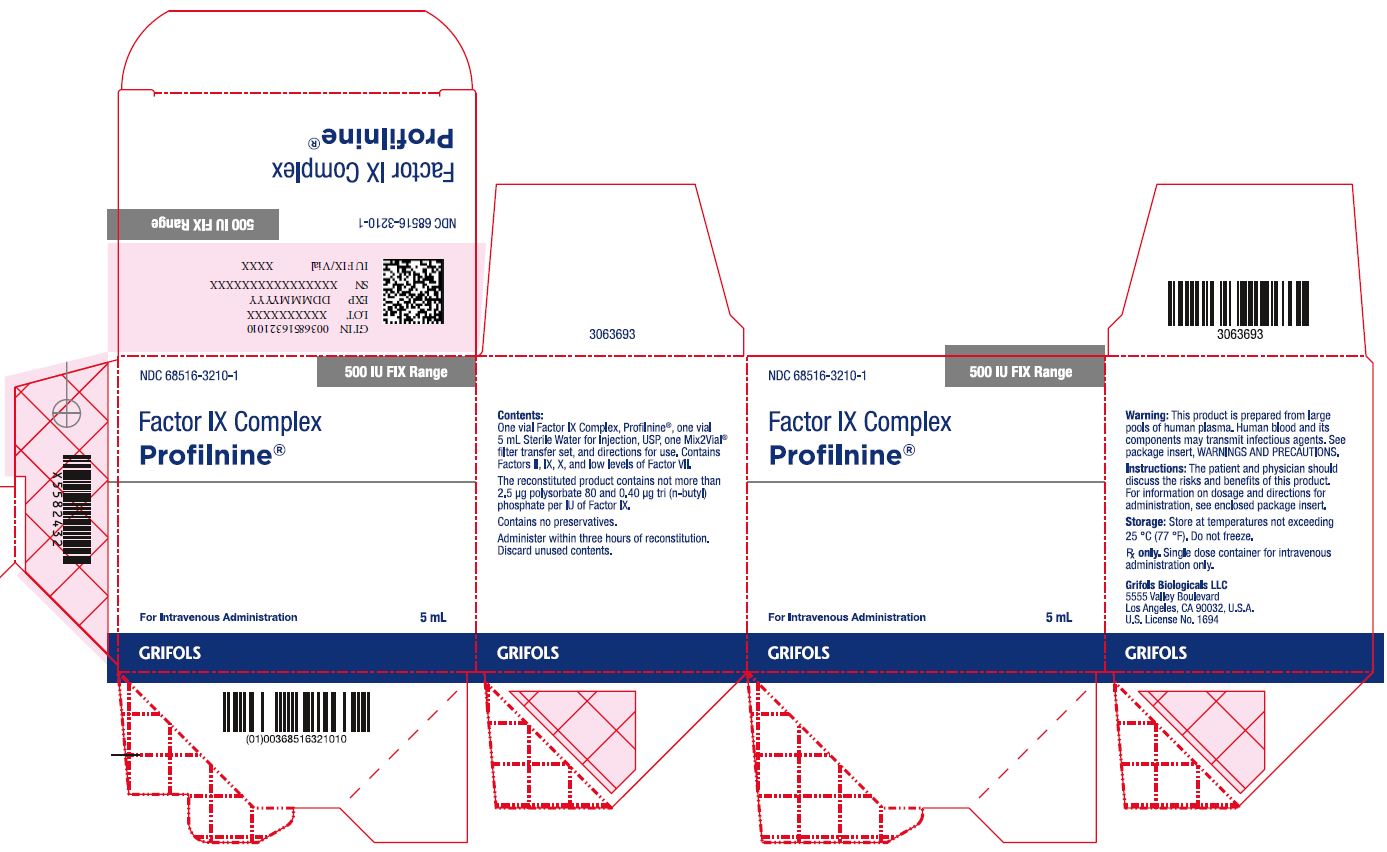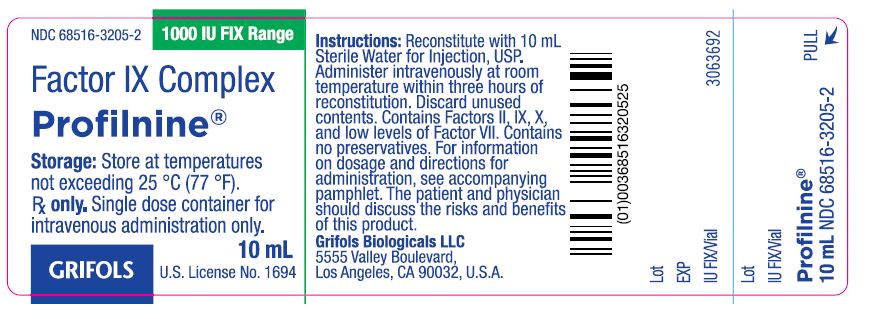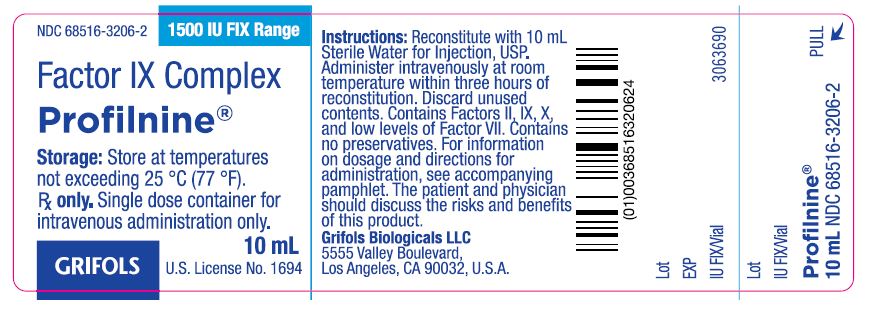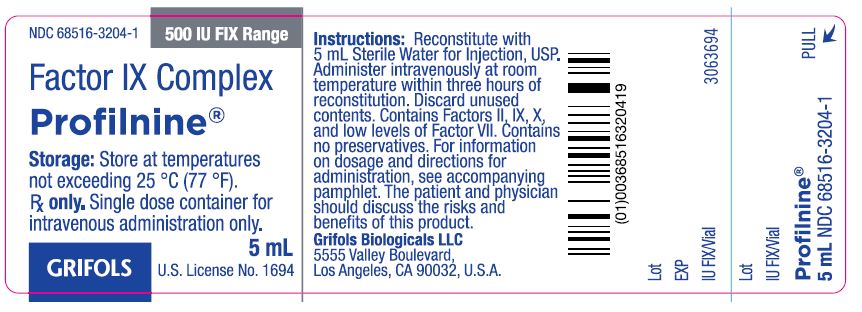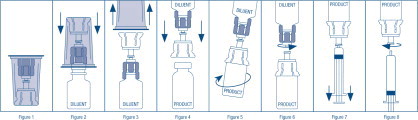 DRUG LABEL: Profilnine
NDC: 68516-3207 | Form: KIT | Route: INTRAVENOUS
Manufacturer: GRIFOLS USA, LLC
Category: other | Type: PLASMA DERIVATIVE
Date: 20250528

ACTIVE INGREDIENTS: factor ix complex 500 [iU]/5 mL; water 1 mL/1 mL
INACTIVE INGREDIENTS: sodium chloride; Sodium Citrate, Unspecified Form; sodium phosphate

Factor IX Complex
Profilnine®

DESCRIPTION

Profilnine®, Factor IX Complex, is a solvent/detergent treated, nanofiltered, sterile, lyophilized concentrate of coagulation factors IX, II, X, and low levels of factor VII. The factor II content is not more than (NMT) 150 units* per 100 factor IX units, the factor X content is NMT 100 units per 100 factor IX units, and the factor VII content is NMT 35 units per 100 factor IX units. Profilnine does not contain heparin and contains no preservatives. Profilnine contains few, if any, activated factors based on results from the non-activated partial thromboplastin time (NAPTT) test^1,2.

Profilnine is intended for intravenous administration only. Each vial is a single-dose container and is labeled with the factor IX potency expressed in International Units.

Profilnine is prepared from pooled human plasma and purified by diethylaminoethyl (DEAE) cellulose adsorption. The risk of transmission of infective agents by Profilnine has been substantially reduced by donor selection procedures and virus screening of individual donations and plasma pools by serological and nucleic acid testing. In addition, virus elimination steps such as nanofiltration^3 and solvent/detergent (tri-n-butyl phosphate) treatment^4 have been incorporated into the Profilnine manufacturing process. Additional removal of some viruses occurs during the DEAE cellulose product purification step.

The ability of the manufacturing process to eliminate virus from Profilnine was evaluated in the laboratory by intentionally adding virus to product just prior to the elimination step and monitoring virus removal. Table 1 shows the amounts of virus that can be removed by solvent/detergent treatment, nanofiltration, and purification by DEAE chromatography when vesicular stomatitis virus (VSV), human immunodeficiency virus-1 and 2 (HIV-1, HIV-2), parvovirus, West Nile virus (WNV), bovine viral diarrhea virus (BVDV), hepatitis A virus (HAV), and pseudorabies virus (PRV) were evaluated in these virus spiking studies. The results indicate that the solvent/detergent treatment step inactivates enveloped viruses and the nanofiltration step removes both enveloped and non-enveloped viruses.

___________________________________
* Unit refers to International Unit in the labeling of Profilnine.

Table 1: Virus Reduction
Virus | Virus Type | Model For: | Virus Reduction (log10)
Virus | Virus Type | Model For: | Process Step
Virus | Virus Type | Model For: | 1st DEAE Chromatography | Solvent-Detergent | Nanofiltration
Sindbis | Env | Hepatitis C | 1.4 | ≥ 5.3 | NT
VSV | Env | Robust enveloped viruses | NT | ≥ 4.9 | NT
HIV-1 | Env | HIV-1 | NT | ≥ 12.2 | ≥ 6.2
HIV-2 | Env | HIV-2 | NT | ≥ 6.0 | NT
WNV | Env | WNV | NT | NT | ≥ 6.6
BVDV | Env | Hepatitis C | NT | NT | ≥ 4.9
Parvo* | Non-Env | Parvovirus B19 | NT | NT | ≥ 6.1
HAV | Non-Env | HAV | NT | NT | ≥ 5.8
PRV | Env | Hepatitis B | NT | NT | ≥ 5.3
* Porcine, NT=Not tested, Env=Enveloped

CLINICAL PHARMACOLOGY

Profilnine is a mixture of the vitamin K-dependent clotting factors IX, II, X, and low levels of VII. The administration of Profilnine temporarily increases the plasma levels of factor IX, thus enabling a temporary correction of the factor deficiency.

A clinical study that evaluated twelve subjects with hemophilia B indicated that, following administration of Profilnine, the factor IX in vivo half-life was 24.68 ± 8.29 hours and recovery was 1.15 ± 0.16 units/dL per unit infused per kg body weight.

Administration of Factor IX Complex can result in higher than normal levels of factor II due to the significantly longer half-life of factor II^5.

INDICATIONS AND USAGE

Profilnine, Factor IX Complex, is indicated for the prevention and control of bleeding in patients with factor IX deficiency (hemophilia B).

Profilnine contains non-therapeutic levels of factor VII and is not indicated for use in the treatment of factor VII deficiency.

CONTRAINDICATIONS

None known.

WARNINGS

Transmissible Infectious Agents

Because Profilnine is made from human blood, it may carry a risk of transmitting infectious agents, e.g., viruses, the variant Creutzfeldt-Jakob disease (vCJD) agent and, theoretically, the Creutzfeldt-Jakob disease (CJD) agent.

Inhibitors

Patients can develop neutralizing antibodies (inhibitors) after treatment with Profilnine. Monitor patients for inhibitors, which should be quantified in Bethesda Units (BU) using appropriate laboratory testing.

Hypersensitivity

Hypersensitivity, including anaphylaxis, has been reported. Inform patients of the early symptoms and signs of hypersensitivity reaction, including hives, generalized urticaria, angioedema, chest tightness, dyspnea, wheezing, faintness, hypotension, tachycardia, and anaphylaxis.

Thrombosis

The use of factor IX complex concentrates has been associated with the development of thromboembolic complications. Patients at increased risk for thrombosis include those undergoing surgery, post surgery, with known liver disease, and with signs of fibrinolysis, thrombosis, or disseminated intravascular coagulation (DIC)^5. When administering Profilnine to these high-risk patients, monitor for early signs of consumptive coagulopathy with appropriate laboratory testing. Only administer Profilnine to patients when the benefits outweigh the risks.

PRECAUTIONS

Vasomotor reactions may result from overly rapid administration. Do not exceed the recommended infusion rate of 10 mL/min.

Information for Patients

Advise patients to report to their physician any decrease in effectiveness of Factor IX treatment, as this can indicate development of inhibitors.

Hypersensitivity, including anaphylaxis, has been reported for factor IX complex concentrate products. Inform patients of the early symptoms and signs of hypersensitivity reaction, including hives, rash, swelling, chest tightness, shortness of breath, wheezing, faintness, decrease in blood pressure, and rapid heartbeat. Advise patients to discontinue use of the product and contact their physician and/or seek immediate emergency care if these symptoms occur.

Pregnancy

Animal reproduction studies have not been conducted with Profilnine. It is also not known whether Profilnine can cause fetal harm when administered to a pregnant woman or can affect reproduction capacity. Only give Profilnine to a pregnant woman if clearly indicated.

Pediatric Use

Safety and effectiveness in pediatric patients have not been established.

Natural Rubber Latex Sensitivity

Certain components used in the packaging of this product contain natural rubber latex. In patients with sensitivity to natural rubber latex, use Profilnine only if needed.

ADVERSE REACTIONS

Adverse reactions with Profilnine may include headache, fever, chills, flushing, nausea, vomiting, tingling, lethargy, urticaria, and manifestations of allergic reactions.

The following adverse reactions have been identified during post-approval use of Profilnine: hypersensitivity reactions including shortness of breath, diaphoresis, and hypotension, as well as thrombosis including pulmonary embolism and deep vein thrombosis, disseminated intravascular coagulation, and inhibitor development. Because these reactions are reported voluntarily from a population of uncertain size, it is not always possible to reliably estimate their frequency or establish a causal relationship to drug exposure.

To report SUSPECTED ADVERSE REACTIONS, contact Grifols at 1-888-GRIFOLS (1-888-474-3657) or FDA at 1-800-FDA-1088 or www.fda.gov/medwatch.

DOSAGE AND ADMINISTRATION

Dose

Each vial of Profilnine is labeled with total units expressed as International Units (IU). According to the WHO International Standard, one unit approximates the activity in one mL of normal plasma.

A 1% increase in factor IX (0.01 units) per unit administered per kg body weight can be expected^1. The amount of Profilnine required to establish hemostasis will vary with each patient and circumstance. Use the following formula and example as guides in determining the number of units to be administered:

Body weight (in kg) | X | Desired increase in Plasma Factor IX (Percent) | X | 1 Units/kg | = | Number of Factor IX Units Required
Example:
50 kg | X | 25 (% increase) | X | 1 Units/kg | = | 1,250 Units of factor IX

Due to variability among patients and their clinical condition, monitor the factor IX level of each patient frequently during replacement therapy.

Table 2 below provides treatment guidelines for hemorrhagic events and surgery in patients with factor IX deficiency.

Table 2: Treatment Guidelines
Type of Bleeding or Surgical Procedure | Factor IX Level Required, % of Normal (Dose) | Frequency of Doses | Duration of Therapy (Days)
Minor to Moderate Hemorrhages | 20-30% (20-30 IU FIX/kg) until hemorrhage stops and healing has been achieved. | Every 16-24 hrs | Minor: 1-2 days Moderate: 2-7 days
Major Hemorrhages | 30-50% (30-50 IU FIX/kg). Following this treatment period, maintain FIX levels at 20% (20 IU FIX/kg) until healing has been achieved. | Every 16-24 hrs | 3-10 days
Surgery | Prior to surgery, 30-50% (30-50 IU FIX/kg). For dental extractions, bring FIX levels to 50% immediately prior to the procedure. Maintain FIX levels at 30-50% (30-50 IU FIX/kg) until healing has been achieved. | Every 16-24 hrs | 7-10 days

Dosing requirements and frequency of dosing are calculated on the basis of an initial response of 1% FIX increase achieved per IU of FIX infused per kg body weight and an average half-life for FIX of 24 hours. If dosing studies reveal that a particular patient exhibits a lower response, monitor blood levels and adjust the dose accordingly.

Reconstitution

Use Aseptic Technique

1. Ensure that concentrate (Profilnine) and diluent (Sterile Water for Injection, USP) are at room temperature (but not above 37° C) before reconstitution.
2. Remove the plastic flip off cap from the diluent vial.
3. Gently swab the exposed stopper surface with a cleansing agent such as alcohol. Avoid leaving any excess cleansing agent on the stopper.
4. Open the Mix2Vial® package by peeling away the lid (Figure 1). Leave the Mix2Vial in the clear outer packaging.
5. Place the diluent vial upright on an even surface, hold the vial tightly, and pick up the Mix2Vial in its clear outer packaging. While holding the diluent vial securely, push the blue end of the Mix2Vial vertically down through the diluent vial stopper (Figure 2).
6. While holding onto the diluent vial, carefully remove the clear outer packaging from the Mix2Vial set, ensuring the Mix2Vial remains attached to the diluent vial (Figure 3).
7. Place the product vial upright on an even surface, invert the diluent vial with the Mix2Vial attached.
8. While holding the product vial securely on a flat surface, push the clear end of the Mix2Vial set vertically down through the product vial stopper (Figure 4). The diluent will automatically transfer out of its vial into the product vial.
  NOTE: If the Mix2Vial is connected at an angle, the vacuum may be released from the product vial and the diluent will not transfer into the product vial.
9. With the diluent and product vials still attached to the Mix2Vial, gently swirl the product vial to ensure the product is fully dissolved (Figure 5). Reconstitution requires less than 10 minutes. Do not shake the vial.
10. Disconnect the Mix2Vial into two separate pieces (Figure 6) by holding each vial adapter and twisting counterclockwise. After separating, discard the diluent vial with the blue end of the Mix2Vial.
11. Draw air into an empty, sterile syringe. Keeping the product vial upright with the clear end of the Mix2Vial attached, screw the disposable syringe onto the luer lock portion of the Mix2Vial device by pressing and twisting clockwise. Inject air into the product vial.
12. While keeping the syringe plunger depressed, invert the system upside down and draw the reconstituted product into the syringe by pulling the plunger back slowly (Figure 7).
13. When the reconstituted product has been transferred into the syringe, firmly hold the barrel of the syringe and the clear vial adapter (keeping the syringe plunger facing down) and unscrew the syringe from the Mix2Vial (Figure 8). Hold the syringe upright and push the plunger until no air is left in the syringe. Attach the syringe to a venipuncture set.
  NOTE: If the same patient is to receive more than one vial of concentrate, the contents of two vials may be drawn into the same syringe through a separate unused Mix2Vial set before attaching to the venipuncture set.
14. After reconstitution, inspect parenteral drug products visually for particulate matter and discoloration prior to administration, whenever solution and container permit. When reconstitution procedure is strictly followed, a few small particles may occasionally remain. The Mix2Vial set will remove particles and the labeled potency will not be reduced.
15. Do not refrigerate after reconstitution. The reconstituted product is stable for 3 hours at room temperature; use as soon as possible within 3 hours after reconstitution.

Administration

For intravenous administration only,

- Inspect the final solution visually for particulate matter and discoloration prior to administration.
- Administer the prepared drug at room temperature within three hours after reconstitution. Prompt administration is recommended to avoid ill effects of any inadvertent bacterial contamination occurring during reconstitution.
- Administer by intravenous injection (plastic disposable syringe only) or infusion at a rate not exceeding 10 mL/minute.
- Discard any unused Profilnine vial contents. Discard administration equipment into the appropriate safety container after single use. Do not resterilize components. Do not reuse components.

HOW SUPPLIED

Profilnine is supplied in sterile lyophilized form in single-dose vials accompanied by a suitable volume of diluent(Sterile Water for Injection, USP), according to factor IX potency. Each vial is labeled with the factor IX potency expressed in International Units which is referenced to the WHO International Standard. Profilnine is packaged with a Mix2Vial filter transfer set for use in administration.

The product is available in several potencies, with carton and vial label color coded based upon assay as follows:

Potency | Carton NDC | Assay Color Code
500 units FIX/5 mL | 68516-3210-1 or 68516-3207-1 | 500 units FIX Range - gray box
1000 units FIX/10 mL | 68516-3211-2 or 68516-3208-2 | 1000 units FIX Range - green box
1500 units FIX/10 mL | 68516-3212-2 or 68516-3209-2 | 1500 units FIX Range - blue box

The diluent vial stopper contains natural rubber latex. All other components of the kit are not made with natural rubber latex.

STORAGE

Profilnine is stable for three years, up to the expiration date printed on its label, provided that the storage temperature does not exceed 25 °C (77 °F). Do not freeze.

Rx only

REFERENCES

1. Menache, D., Roberts, H.R. Summary report and recommendations of the task force members and consultants. Thromb Diath Haemorrh 33:645-647, 1975.
2. Kingdon, H.S., Lundblad, R.L., Veltkamp, J.J., Aronson, D.L. Potentially thrombogenic materials in Factor IX Concentrates. Thromb Diath Haemorrh 33:617- 631, 1975.
3. Burnouf T, Radosevich M. Nanofiltration of plasma-derived biopharmaceutical products. Haemophilia : the official journal of the World Federation of Hemophilia. 2003;9:24-37.
4. Dichtelmüller HO, Biesert L, Fabbrizzi F, Gajardo R, Gröner A, von Hoegen I, Jorquera JI, Kempf C, Kreil TR, Pifat D, Osheroff W, Poelsler G. Robustness of solvent/detergent treatment of plasma derivatives: a data collection from Plasma Protein Therapeutics Association member companies. Transfusion 49:1931-1943, 2009.
5. Sorensen, B., Spahn, D.R., Innerhofer, P., Spannagl, M., Rossaint, R. Clinical review: prothrombin complex concentrates-evaluation of safety and thrombogenicity. Critical Care 15: 201-209, 2011.

Manufactured by:
Grifols Biologicals LLC
5555 Valley Boulevard
Los Angeles, CA 90032, U.S.A.
U.S. License No. 1694
DATE OF REVISION: November 2022

3063695

Principal Display Panel – 500 IU Vial Label

NDC 68516-3204- 1 500 IU FIX Range
Factor IX Complex
Profilnine®
Storage: Store at temperatures
not exceeding 25 °C (77 °F).
Rx Only. Single dose container for
intravenous administration only.
5 mL
GRIFOLS U.S. License No. 1694
Instructions: Reconstitute with
5 mL Sterile Water for Injection, USP.
Administer intravenously at room
temperature within three hours of
reconstitution. Discard unused
contents. Contains Factors II, IX, X,
and low levels of Factor VII. Contains
no preservatives. For information
on dosage and directions for
administration, see accompanying
pamphlet. The patient and physician
should discuss the risks and
benefits of this product.
Grifols Biologicals LLC
5555 Valley Boulevard,
Los Angeles, CA 90032, U.S.A.
Lot
EXP
IU FIX/Vial 3063694
Lot
IU FIX/Vial
Profilnine®
5 mL NDC 68516-3204-1

Principal Display Panel 500 IU Carton Label

NDC 68516-3210-1 500 IU FIX Range
Factor IX Complex
Profilnine®
For Intravenous Administration 5 mL
GRIFOLS
Contents:
One vial Factor IX Complex, Profilnine®, one vial
5 mL Sterile Water for Injection, USP, one Mix2Vial®
filter transfer set, and directions for use. Contains
Factors II, IX, X and low levels of Factor VII.
The reconstituted product contains not more than
2.5 µg polysorbate 80 and 0.40 µg tri (n-butyl)
phosphate per IU of Factor IX.
Contains no preservatives.
Administer within three hours of reconstitution.
Discard unused contents.
GRIFOLS
Warning: This product is prepared from large
pools of human plasma. Human blood and its
components may transmit infectious agents. See
package insert, WARNINGS AND PRECAUTIONS.
Instructions: The patient and physician should
discuss the risks and benefits of this product.
For information on dosage and directions for
administration, see enclosed package insert.
Storage: Store at temperatures not exceeding
25 °C (77 °F). Do not freeze.
Rx only. Single dose container for intravenous
administration only.
Grifols Biologicals LLC
5555 Valley Boulevard
Los Angeles, CA 90032, U.S.A.
U.S. License No. 1694
GRIFOLS
GTIN 00368516321010
LOT XXXXXXXXXX
EXP DDMMMYYYY
SN XXXXXXXX XXXXXXXX
IU FIX/Vial XXXX
3063693

Principal Display Panel – 1000 IU Vial Label
NDC 68516-3205-2 1000 IU FIX Range
Factor IX Complex
Profilnine®
Storage: Store at temperatures
not exceeding 25 °C (77 °F).
Rx Only. Single dose container for
intravenous administration only.
GRIFOLS
10 mL U.S. License No. 1694
Instructions: Reconstitute with 10 mL
Sterile Water for Injection, USP.
Administer intravenously at room
temperature within three hours of
reconstitution. Discard unused
contents. Contains Factors II, IX, X,
and low levels of Factor VII. Contains
no preservatives. For information
on dosage and directions for
administration, see accompanying
pamphlet. The patient and physician
should discuss the risks and
benefits of this product.
Grifols Biologicals LLC
5555 Valley Boulevard,
Los Angeles, CA 90032, U.S.A.
Lot
EXP
IU FIX/Vial 3063692
Lot
IU FIX/Vial
Profilnine®
10 mL NDC 68516-3205-2

Principal Display Panel 1000 IU Carton Label

NDC 68516-3211-2 1000 IU FIX Range
Factor IX Complex
Profilnine®
For Intravenous Administration 10 mL
GRIFOLS
Contents: One vial Factor IX Complex, Profilnine®, one vial
10 mL Sterile Water for Injection, USP, one Mix2Vial®
filter transfer set, and directions for use. Contains
Factors II, IX, X and low levels of Factor VII.
The reconstituted product contains not more than
2.5 µg polysorbate 80 and 0.40 µg tri (n-butyl)
phosphate per IU of Factor IX.
Contains no preservatives.
Administer within three hours of reconstitution.
Discard unused contents.
GRIFOLS
Warning: This product is prepared from large
pools of human plasma. Human blood and its
components may transmit infectious agents. See
package insert, WARNINGS AND PRECAUTIONS.
Instructions: The patient and physician should
discuss the risks and benefits of this product.
For information on dosage and directions for
administration, see enclosed package insert.
Storage: Store at temperatures not exceeding
25 °C (77 °F). Do not freeze.
Rx only Single dose container for intravenous
administration only.
Grifols Biologicals LLC
5555 Valley Boulevard
Los Angeles, CA 90032, U.S.A.
U.S. License No. 1694
GRIFOLS
GTIN 00368516321126
LOT XXXXXXXXXX
EXP DDMMMYYYY
SN XXXXXXXXXXXXXXXX
IU FIX/Vial XXXX
3063691

Principal Display Panel – 1500 IU Vial Label
NDC 68516-3206-2 1500 IU FIX Range
Factor IX Complex
Profilnine®
Storage: Store at temperatures
not exceeding 25 °C (77 °F).
Rx Only. Single dose container for
intravenous administration only.
10 mL
GRIFOLS U.S. License No. 1694
Instructions: Reconstitute with 10 mL
Sterile Water for Injection, USP.
Administer intravenously at room
temperature within three hours of
reconstitution. Discard unused
contents. Contains Factors II, IX, X,
and low levels of Factor VII. Contains
no preservatives. For information
on dosage and directions for
administration, see accompanying
pamphlet. The patient and physician
should discuss the risks and
benefits of this product.
Grifols Biologicals LLC
5555 Valley Boulevard,
Los Angeles, CA 90032, U.S.A.
Lot
EXP
IU FIX/Vial 3063690
Lot
IU FIX/Vial
Profilnine®
10 mL NDC 68516-3206-2

Principal Display Panel 1500 IU Carton Label

NDC 68516-3212-2 1500 IU FIX Range
Factor IX Complex
Profilnine®
For Intravenous Administration 10 mL
GRIFOLS
Contents: One vial Factor IX Complex, Profilnine®, one vial
10 mL Sterile Water for Injection, USP, one Mix2Vial®
filter transfer set, and directions for use. Contains
Factors II, IX, X and low levels of Factor VII.
The reconstituted product contains not more than
2.5 µg polysorbate 80 and 0.40 µg tri (n-butyl)
phosphate per IU of Factor IX.
Contains no preservatives.
Administer within three hours of reconstitution.
Discard unused contents.
Warning: This product is prepared from large
pools of human plasma. Human blood and its
components may transmit infectious agents. See
package insert, WARNINGS AND PRECAUTIONS.
GRIFOLS
Instructions: The patient and physician should
discuss the risks and benefits of this product.
For information on dosage and directions for
administration, see enclosed package insert.
Storage: Store at temperatures not exceeding
25 °C (77 °F). Do not freeze.
Rx only. Single dose container for intravenous
administration only.
Grifols Biologicals LLC
5555 Valley Boulevard
Los Angeles, CA 90032, U.S.A.
U.S. License No. 1694
GRIFOLS
GTIN 00368516321225
LOT XXXXXXXXXX
EXP DDMMMYYYY
SN XXXXXXXXXXXXXXXX
IU FIX/Vial XXXX
3063689

Principal Display Panel - 5 mL Vial Label
NDC 76297-002-02
Sterile Water for Injection, USP
5 mL
Rx Only
For reconstitution of accompanying product
Single-Dose Container, Nonpyrogenic
Do not use unless clear.
No antimicrobial agent or other substance has been added.
Do not use for intravascular injection without making approximately isotonic by addition of suitable solute.
Discard unused portion.
Mfd by: Laboratorios Grifols, S. A. Parets del Vallès,
Barcelona 08150 Spain
Lot
EXP
3057422

Principal Display Panel - 10 mL Vial Label
NDC 76297-002-12
Sterile Water for Injection, USP
10 mL
Rx Only
For reconstitution of accompanying product
Single-Dose Container, Nonpyrogenic
Do not use unless clear.
No antimicrobial agent or other substance has been added.
Do not use for intravascular injection without making approximately isotonic by addition of suitable solute.
Discard unused portion.
Mfd by: Laboratorios Grifols, S. A. Parets del Vallès,
Barcelona 08150 Spain
Lot
EXP
3057423